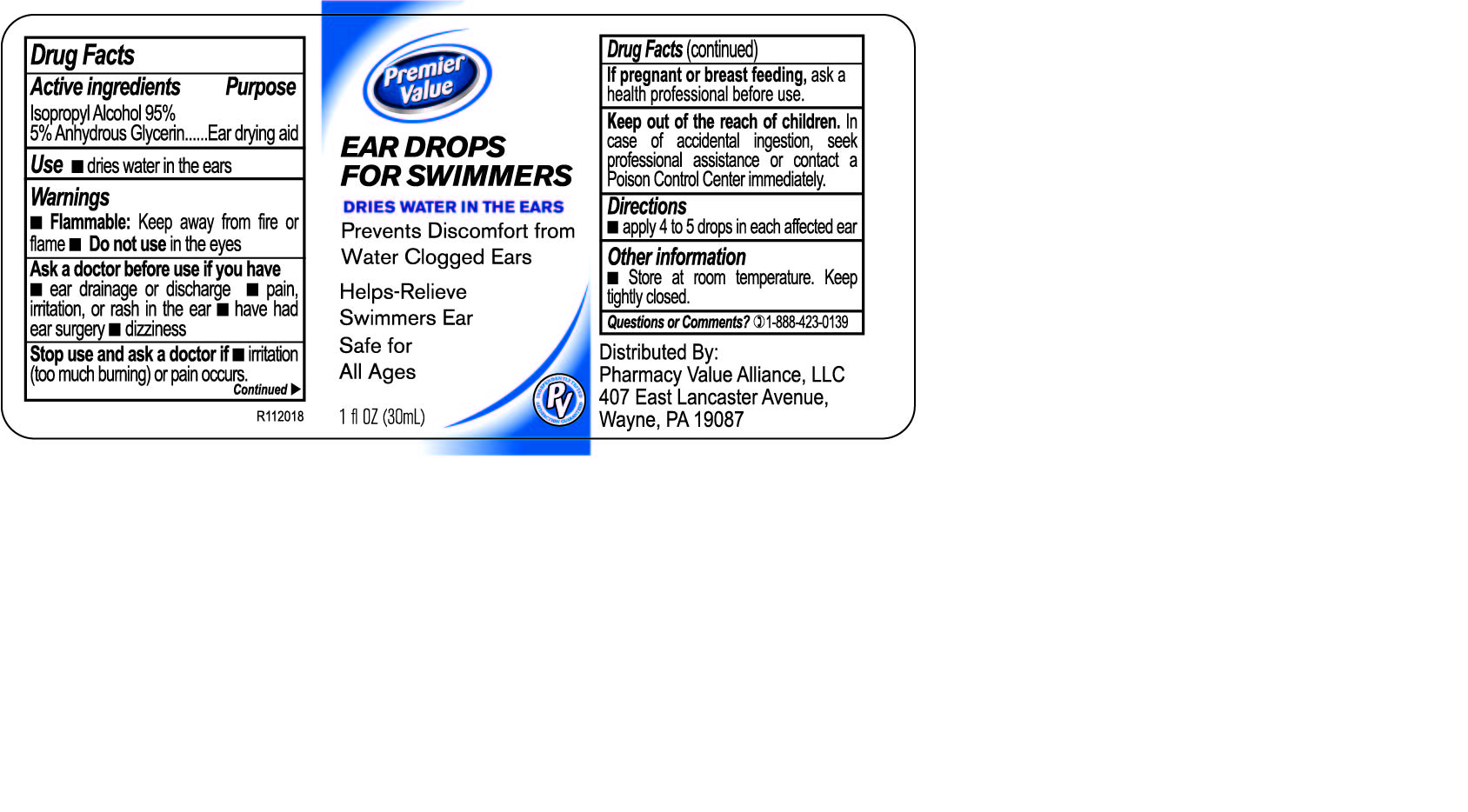 DRUG LABEL: Premiere Value Ear Drops for Swimmers
NDC: 68016-820 | Form: LIQUID
Manufacturer: Pharmacy Value Alliance; LLC
Category: otc | Type: HUMAN OTC DRUG LABEL
Date: 20231220

ACTIVE INGREDIENTS: ISOPROPYL ALCOHOL 950 mg/1 mL
INACTIVE INGREDIENTS: GLYCERIN

Premiere Value Ear Drops for Swimmers

CVS Ear Drops for Swimmers

Drug Facts

Active Ingredient

Isopropyl Alcohol 95% in anhydrous glycerin

Purpose

Ear drying aid

Use

Dries water in the ears.

Warnings

Flammable: Keep away from fire and flame.

Do not use

in the eyes.

Ask a doctor before use if you have

Ear drainage or discharge.

Pain, irritation, or rash in the ear.

Have had ear surgery.

Dizziness.

Stop use and ask doctor if

Irritation (too much burning) or pain occurs.

Keep out of reach of children.

- In case of accidental ingestion, seek professional assistant or contact a Poison Control Center immediately.

Directions

Apply 5 to 5 drops in each affected ear..

Other information

Store at room temperature.

Keep tightly closed.

Inactive Ingredient

Glycerin